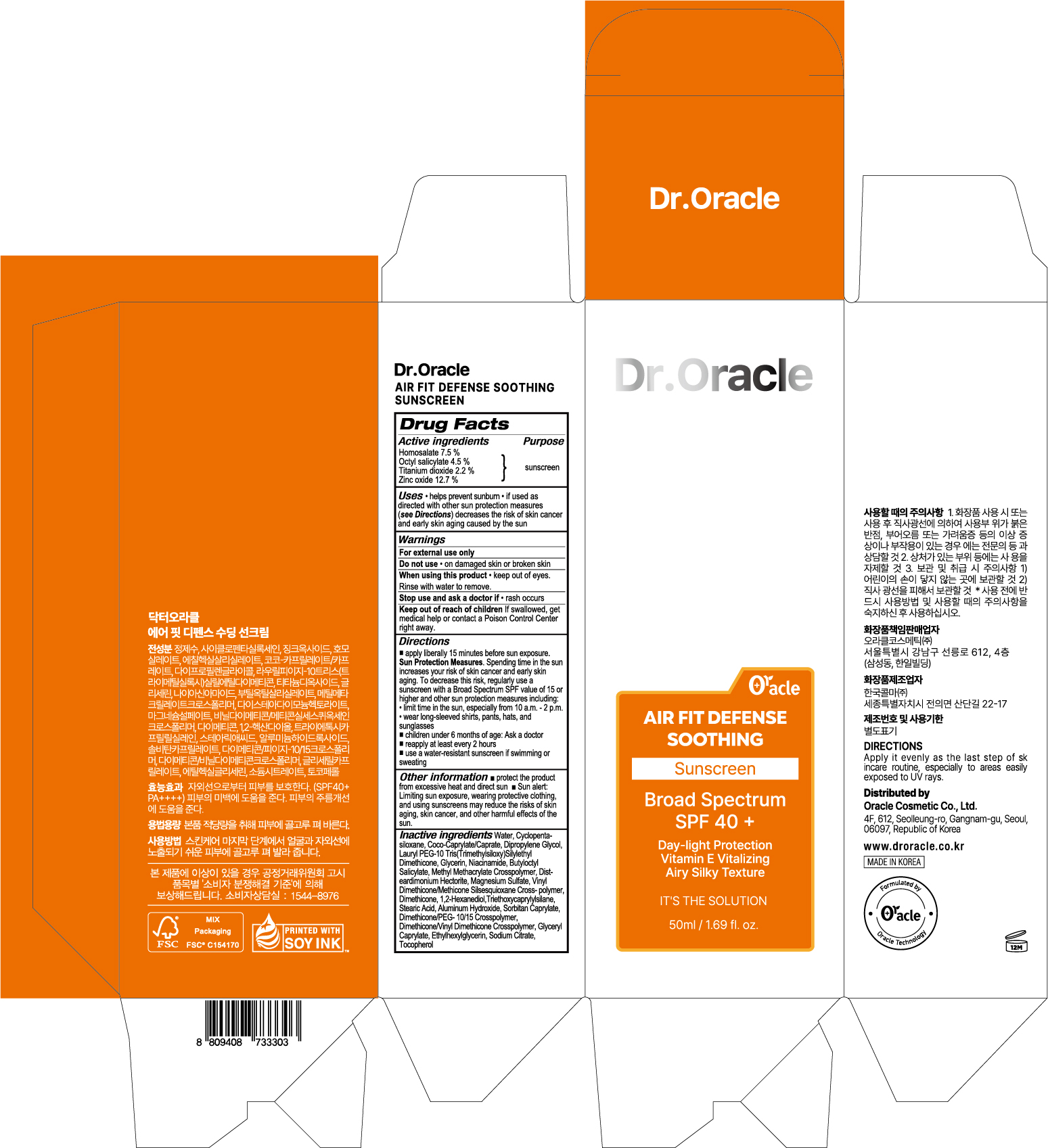 DRUG LABEL: Dr.Oracle AIR FIT DEFENSE SOOTHING SUNSCREEN
NDC: 71883-050 | Form: CREAM
Manufacturer: Oracle Cosmetic Co., Ltd.
Category: otc | Type: HUMAN OTC DRUG LABEL
Date: 20260202

ACTIVE INGREDIENTS: ZINC OXIDE 6.35 g/50 mL; OCTISALATE 2.25 g/50 mL; TITANIUM DIOXIDE 1.1 g/50 mL; HOMOSALATE 3.75 g/50 mL
INACTIVE INGREDIENTS: TRIETHOXYCAPRYLYLSILANE; ALUMINUM HYDROXIDE; ETHYLHEXYLGLYCERIN; SODIUM CITRATE; CYCLOMETHICONE 5; STEARIC ACID; SORBITAN MONOCAPRYLATE; GLYCERYL CAPRYLATE; COCOYL CAPRYLOCAPRATE; GLYCERIN; NIACINAMIDE; BUTYLOCTYL SALICYLATE; MAGNESIUM SULFATE, UNSPECIFIED FORM; 1,2-HEXANEDIOL; TOCOPHEROL; VINYL DIMETHICONE/METHICONE SILSESQUIOXANE CROSSPOLYMER; DIMETHICONE/PEG-10/15 CROSSPOLYMER; WATER; DIMETHICONE; DIPROPYLENE GLYCOL; DISTEARDIMONIUM HECTORITE

Dr.Oracle AIR FIT DEFENSE SOOTHING SUNSCREEN

Active ingredients

Homosalate 7.5 %

Octyl salicylate 4.5 %

Titanium dioxide 2.2 %

Zinc oxide 12.7 %

Purpose

sunscreen

Uses

• helps prevent sunburn • if used as directed with other sun protection measures (see Directions) decreases the risk of skin cancer and early skin aging caused by the sun

Warnings

For external use only

Do not use

• on damaged skin or broken skin

When using this product

• keep out of eyes. Rinse with water to remove.

Stop use and ask a doctor if

• rash occurs

Keep out of reach of children

If swallowed, get medical help or contact a Poison Control Center right away.

Directions

■ apply liberally 15 minutes before sun exposure. Sun Protection Measures. Spending time in the sun increases your risk of skin cancer and early skin aging. To decrease this risk, regularly use a sunscreen with a Broad Spectrum SPF value of 15 or higher and other sun protection measures including:
• limit time in the sun, especially from 10 a.m. - 2 p.m.
• wear long-sleeved shirts, pants, hats, and sunglasses
■ children under 6 months of age: Ask a doctor
■ reapply at least every 2 hours
■ use a water-resistant sunscreen if swimming or sweating

Other information

■ protect the product from excessive heat and direct sun ■ Sun alert: Limiting sun exposure, wearing protective clothing, and using sunscreens may reduce the risks of skin aging, skin cancer, and other harmful effects of the sun.

Inactive ingredients

Water, Cyclopentasiloxane, Coco-Caprylate/Caprate, Dipropylene Glycol, Lauryl PEG-10 Tris(Trimethylsiloxy)Silylethyl Dimethicone, Glycerin, Niacinamide, Butyloctyl Salicylate, Methyl Methacrylate Crosspolymer, Dist- eardimonium Hectorite, Magnesium Sulfate, Vinyl Dimethicone/Methicone Silsesquioxane Cross- polymer, Dimethicone, 1,2-Hexanediol,Triethoxycaprylylsilane, Stearic Acid, Aluminum Hydroxide, Sorbitan Caprylate, Dimethicone/PEG- 10/15 Crosspolymer, Dimethicone/Vinyl Dimethicone Crosspolymer, Glyceryl Caprylate, Ethylhexylglycerin, Sodium Citrate, Tocopherol